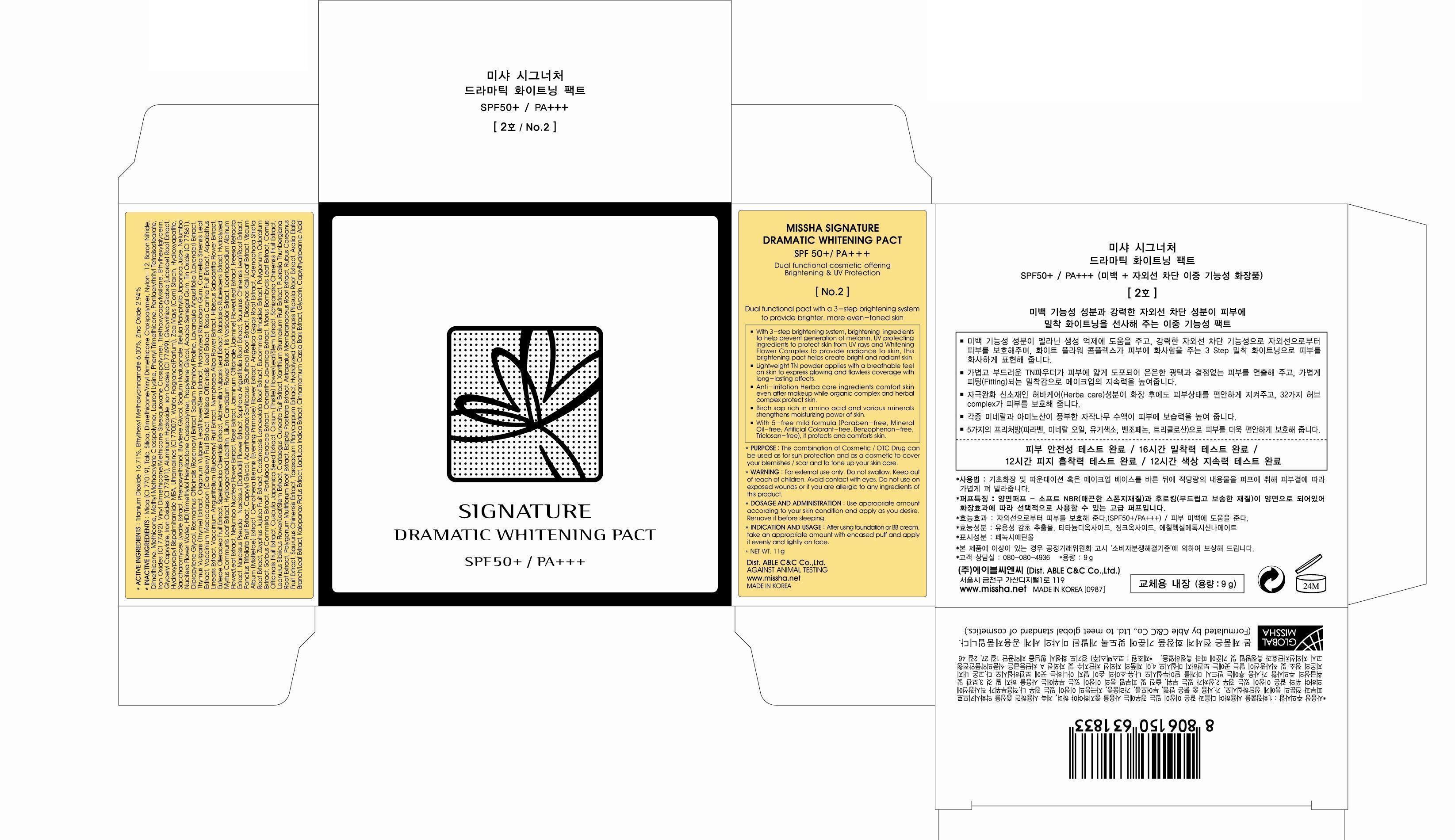 DRUG LABEL: MISSHA SIGNATURE DRAMATIC WHITENING PACT
NDC: 13733-015 | Form: POWDER
Manufacturer: ABLE C&C CO., LTD.
Category: otc | Type: HUMAN OTC DRUG LABEL
Date: 20121025

ACTIVE INGREDIENTS: TITANIUM DIOXIDE 1.84 g/11 g; OCTINOXATE 0.66 g/11 g; ZINC OXIDE 0.32 g/11 g
INACTIVE INGREDIENTS: Dimethicone; Glyceryl Caprylate; Water; Butylene Glycol

ACTIVE INGREDIENT

ACTIVE INGREDIENTS:
Titanium Dioxide 16.71%, Ethylhexyl Methoxycinnamate 6.00%, Zinc Oxide 2.94%

INACTIVE INGREDIENT

INACTIVE INGREDIENTS:
Mica, Talc, Silica, Dimethicone/Vinyl Dimethicone Crosspolymer, Nylon-12, Boron Nitride, Dimethicone, Methicone, Methyl Methacrylate Crosspolymer, Lauroyl Lysine, Phenyl Trimethicone, Pentaerythrityl Tetraisostearate, Iron Oxides, Vinyl Dimethicone/Methicone Silsesquioxane Crosspolymer, Triethoxycaprylylsilane, Ethylhexylglycerin, Glyceryl Caprylate, Aluminum Hydroxide, Glycyrrhiza Glabra (Licorice) Root Extract, Hydroxypropyl Bispalmitamide MEA, Ultramarines (CI 77007), Water, Fragrance(Parfum), Zea Mays (Corn) Starch, Hydroxyapatite, Saccharomyces Lysate Extract, Phenoxyethanol, Butylene Glycol, Sodium Hyaluronate, Betula Platyphylla Japonica Juice, Nelumbo Nucifera Flower Water, HDI/Trimethylol Hexyllactone Crosspolymer, Propylene Glycol, Acacia Senegal Gum, Tin Oxide, Dipropylene Glycol, Rosmarinus Officinalis (Rosemary) Extract, Sodium Palmitoyl Proline, Lavandula Angustifolia (Lavender) Extract, Thymus Vulgaris (Thyme) Extract, Origanum Vulgare Leaf/Flower/Stem Extract, Hydrolyzed Rhizobian Gum, Camellia Sinensis Leaf Extract, Vaccinium Macrocarpon (Cranberry) Fruit Extract, Melissa Officinalis Leaf Extract, Rosa Canina Fruit Extract, Aspalathus Linearis Extract, Vaccinium Angustifolium (Blueberry) Fruit Extract, Nymphaea Alba Flower Extract, Hibiscus Sabdariffa Flower Extract, Euterpe Oleracea Fruit Extract, Sigesbeckia Orientalis Extract, Alchemilla Vulgaris Leaf Extract, Rabdosia Rubescens Extract, Hydrolyzed Myrtus Communis Leaf Extract, Hydrogenated Lecithin, Lilium Candidum Flower Extract, Iris Versicolor Extract, Leontopodium Alpinum Flower/Leaf Extract, Nelumbo Nucifera Flower Extract, Rose Extract, Jasminum Officinale (Jasmine) Flower/Leaf Extract, Freesia Refracta Extract, Narcissus Pseudo-Narcissus (Daffodil) Flower Extract, Sophora Angustifolia Root Extract, Saururus Chinensis Leaf/Root Extract, Poncirus Trifoliata Fruit Extract, Caprylyl Glycol, Acanthopanax Senticosus (Eleuthero) Root Extract, Diospyros Kaki Leaf Extract, Viscum Album (Mistletoe) Extract, Oenothera Biennis (Evening Primrose) Flower Extract, Angelica Gigas Root Extract, Adenophora Stricta Root Extract, Zizyphus Jujuba Fruit Extract, Codonopsis Lanceolata Root Extract, Eucommia Ulmoides Extract, Polygonum Odoratum Extract, Sorbus Commixta Extract, Portulaca Oleracea Extract, Oenanthe Javanica Extract, Morus Bombycis Leaf Extract, Cornus Officinalis Fruit Extract, Cuscuta Japonica Seed Extract, Cirsium (Thistle) Flower/Leaf/Stem Extract, Schizandra Chinensis Fruit Extract, Leonurus Sibiricus Flower/Leaf/Stem Extract, Crataegus Cuneata Fruit Extract, Xanthium Strumarium Fruit Extract, Pueraria Thunbergiana Root Extract, Polygonum Multiflorum Root Extract, Eclipta Prostrata Extract, Astragalus Membranaceus Root Extract, Rubus Coreanus Fruit Extract, Saururus Chinensis Extract, Taraxacum Platycarpum Extract, Hydrolyzed Codonopsis Pilosula Root Extract, Aralia Elata Branch/Leaf Extract, Kalopanax Pictus Extract, Lactuca Indica Extract, Cinnamomum Cassia Bark Extract, Glycerin, Caprylhydroxamic Acid

PURPOSE

This combination of Cosmetic / OTC Drug can be used as for sun protection and as a cosmetic to cover your blemishes, scar and to tone up your skin care.

WARNINGS

WARNING:
For external use only.
Do not swallow.
Keep out of reach of children.
Avoid contact with eyes.
Do not use on exposed wounds or if you are allergic to any ingredients of this product

KEEP OUT OF REACH OF CHILDREN

INDICATIONS AND USAGE

INDICATION AND USAGE:
After using foundation or BB cream, take an appropriate amount with encased puff and apply it evenly and lightly on face.

DOSAGE AND ADMINISTRATION

Use appropriate amount according to your skin condition and apply as you desire.
Remove it before sleeping.